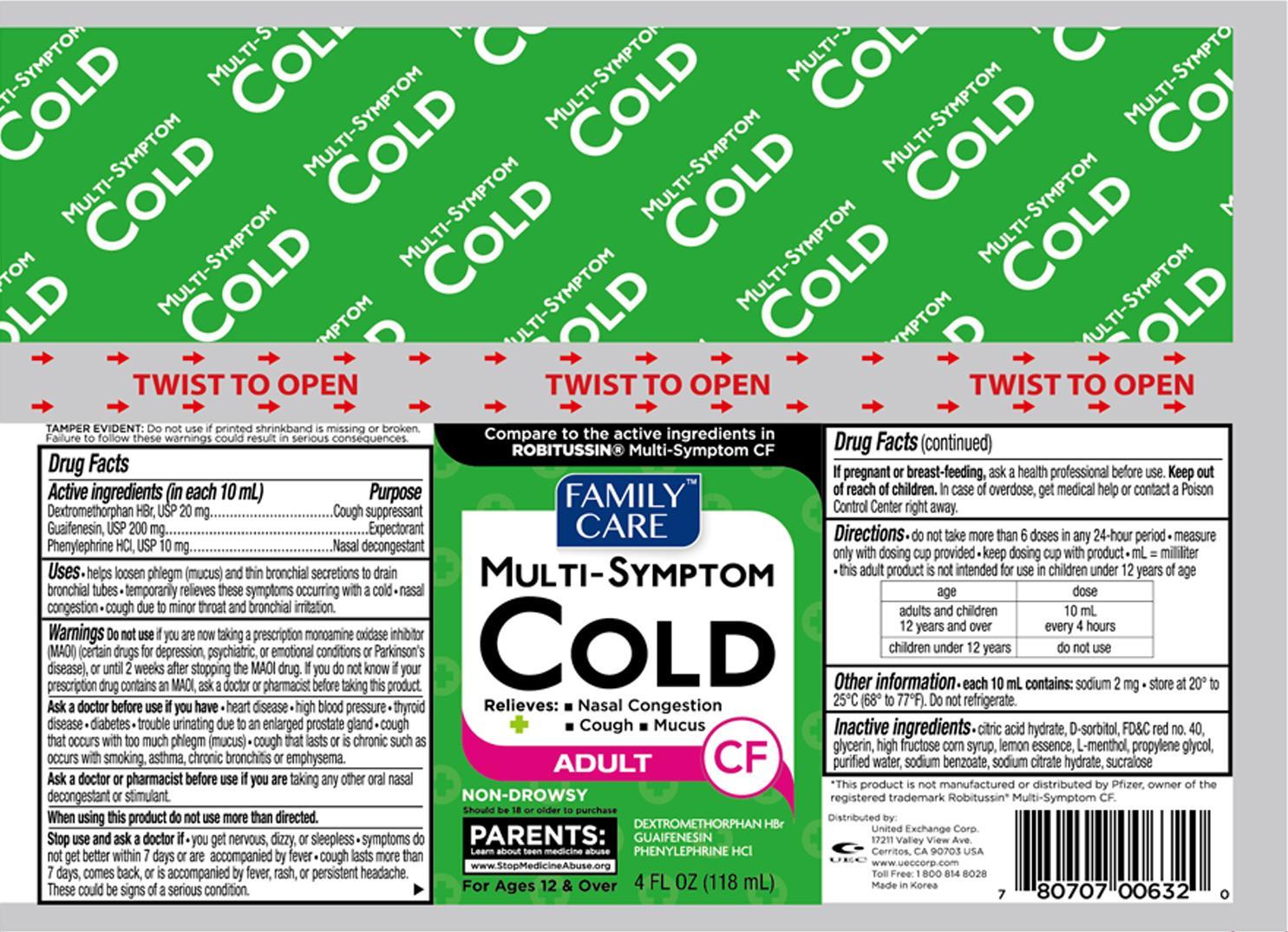 DRUG LABEL: Family Care Multi Symptom Cold
NDC: 65923-632 | Form: LIQUID
Manufacturer: United Exchange Corp.
Category: otc | Type: HUMAN OTC DRUG LABEL
Date: 20150731

ACTIVE INGREDIENTS: DEXTROMETHORPHAN HYDROBROMIDE 10 mg/5 mL; GUAIFENESIN 100 mg/5 mL; PHENYLEPHRINE HYDROCHLORIDE 5 mg/5 mL
INACTIVE INGREDIENTS: CITRIC ACID MONOHYDRATE; SORBITOL; FD&C RED NO. 40; GLYCERIN; HIGH FRUCTOSE CORN SYRUP; MENTHOL; PROPYLENE GLYCOL; WATER; SODIUM BENZOATE; SUCRALOSE

Active ingredient (in each 10 mL) Purpose

Gextromethorphan HBr, USP 20 mg.............................Cough suppressant

Guaifenesin, USP 200 mg......................................................Expectorant

Phenylephrine HCI, USP 10 mg....................................Nasal decongestant

Uses

- helps loosen phlegm (mucus) and thin bronchial secretions to drain bronchial tubes
- temporarily relieves these symptoms occuring with a cold
- nasal congestion
- cough due to minor throat and bronchial irritation.

Warnings

Do not use if you are now taking a prescription monoamine oxidase inhibitor (MAOI) (certain drugs for depression, psychiatric, or emotional conditions or Parkinson's disease), or until 2 weeks after stopping the MAOI drug. If you do not know if your prescription drug contains an MAOI, ask a doctor or pharmacist before taking this product.

Ask a doctor or pharmacist before us if you are taking any other oral nasal decongestant or stimulant.

When using this product do not use more than directed.

Stop use and ask a doctor if

- you get nervous, dizzy, or sleepless
- symptoms do not get better within 7 days or are accompanied by fever
- cough lasts more than 7 days comes back, or is accompanied by fever, rash, or persistent headache. These could be signs of a serious condition.

PREGNANCY OR BREAST FEEDING

If pregnant or breast-feeding, ask a health professional before use.

Keep out of reach of children. In case of overdose, get medical help or contact a Poison Control Center right away.

Directions

- do not take more than 6 doses in any 24-hour period
- measure only with dosing cup provided
- keep dosing cup with product
- mL=milliliter
- this adult product is not intended for use in children under 12 years of age

age | dose
adults and children 12 years and over | 10 mL every 4 hours
children under 12 years | do not use

Other information

- each 10 mL contains: sodium 2 mg
- store at 20° to 25°C (68° to 77°F)
- Do not refrigerate

Inactive ingredients

citric acid hydrate, D-sorbitol, FD&C red no. 40, glycerin, high fructose corn syrup, lemon essence, L-menthol, propylene glycol, purified water, sodium benzoate, sodium citrate hydrate, sucralose

DOSAGE AND ADMINISTRATION

Distribued by:

United Exchange Corp.

17211 Valley View Ave.

Cerritos, CA 90703 U.S.A

Made in Korea